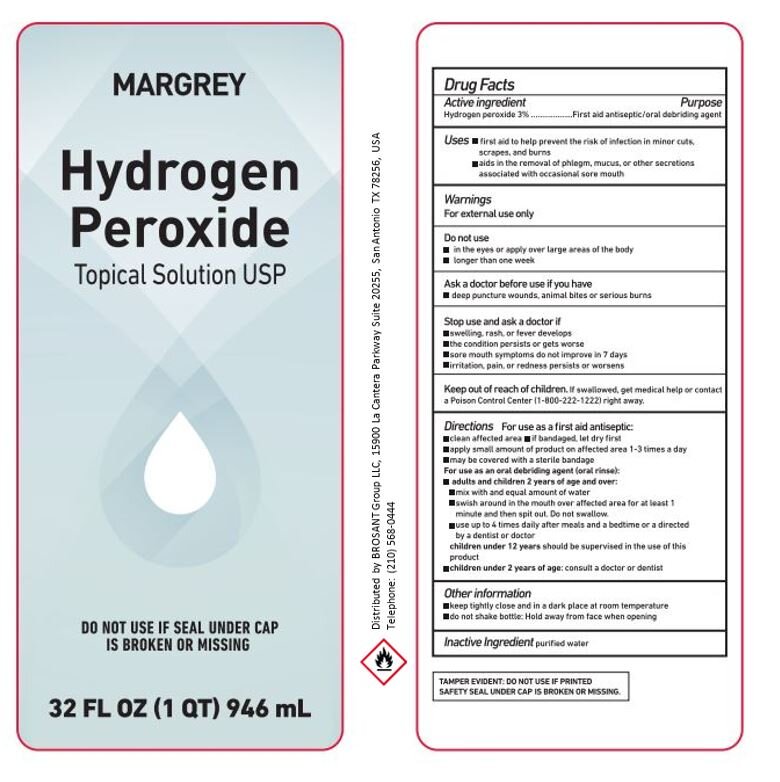 DRUG LABEL: hydrogen peroxide
NDC: 77210-0035 | Form: LIQUID
Manufacturer: EXPORTADORA IN AND OUT S DE RL DE CV
Category: otc | Type: HUMAN OTC DRUG LABEL
Date: 20221017

ACTIVE INGREDIENTS: HYDROGEN PEROXIDE 3 mL/100 mL
INACTIVE INGREDIENTS: WATER 70 mL/100 mL

Active ingredient

Hydrogen peroxide 3%

Purpose

First aid antiseptic/oral debriding agent

USES

-First aid to help prevent the risk of infection in minor cuts, scraps and burns

WARNING

For external use only

DO NOT USE

-in the eyes or apply over large areas of the body
-longer than one week

Ask a doctor before use if you have

-deep puncture wounds, animal bites or serious burns

STOP USE AND ASK A DOCTOR IF

-swelling, rash or fever develops
-the condition persists or gets worse
-sore mouth symptoms do not improve in 7 days
-irritation, pain, or redness persists or worsen

KEEP OUT OF REACH OF CHILDREN

If swallowed, get medical help or contact a poison control center (1-800-222-1222) right away

DIRECTIONS

For use as a first aid antiseptic:
-clean affected area
-if bandaged, let dry first
-apply small amount of product on affected area 1-3 times a day
-may be covered with a sterile bandage
For use as an oral debriding agent (oral rinse)
-adults and children 2 years of age and over
-mix with and equal amount of water
-swish around in the mouth over affected area for at least 1 minute and then spit out. Do not swallow
-use up to 4 times daily after meals and bedtime or a directed by a dentist or doctor
children under 12 years should be supervised in the use of this product
children under 2 years of age: consult a doctor or dentist

OTHER INFORMATION

-keep tightly close and in a dark place at room temperature
-do not shake bottle: hold away from face when opening

INACTIVE INGREDIENT

Purified water

Principal Display

Margrey
Hydrogen peroxide
Topical solution USP
Do not use if seal under cap
is broken or missing
32FL OZ 946ml
Distributed by BROSANT Group LLC, 15900 La cantera Parkway Suite 20255, San Antonio TX 78256, USA
Telephone: (210) 568-0444